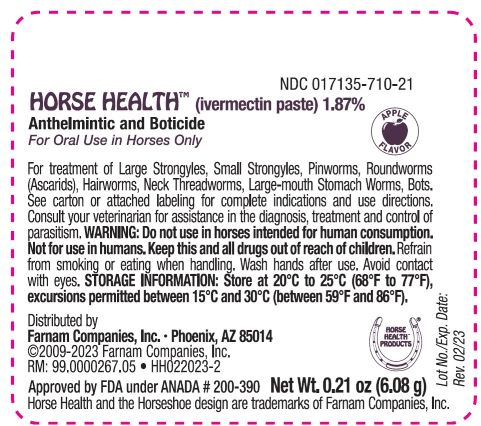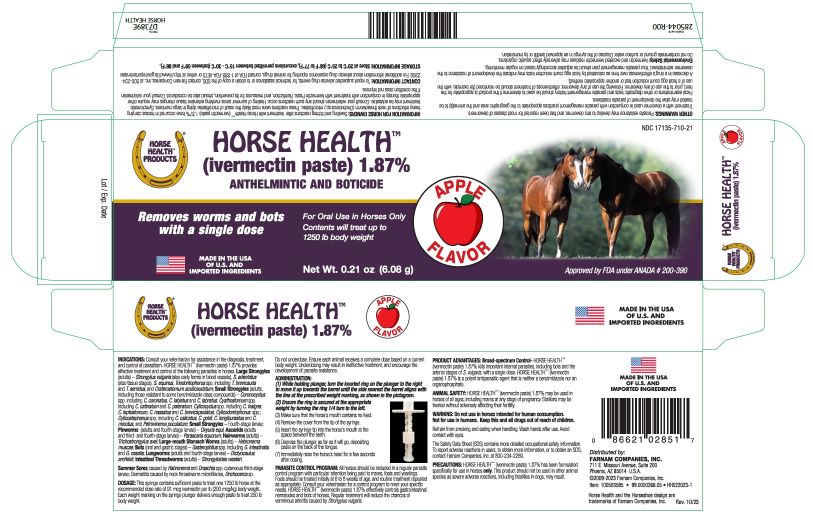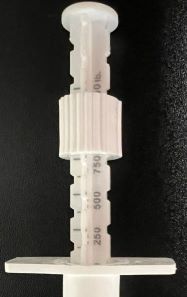 DRUG LABEL: Horse Health
NDC: 17135-710 | Form: PASTE
Manufacturer: Farnam Companies, Inc.
Category: animal | Type: OTC ANIMAL DRUG LABEL
Date: 20250902

ACTIVE INGREDIENTS: Ivermectin 1.87 g/100 g

Ivermectin Paste

INDICATIONS AND USAGE

Approved by FDA under ANADA # 200-390 NDC 17135-710-21

HORSE HEALTH (ivermectin paste) 1.87%
Anthelmintic and Boticide
For Oral Use in Horses Only

Contents will treat up to 1250 lb body weight.
Removes worms and bots with a single dose.

Each Syringe Contains 0.21 oz (6.08 g) HORSE HEALTH (ivermectin paste) 1.87%
INDICATIONS: Consult your veterinarian for assistance in the diagnosis, treatment, and control of parasitism. Horse Health (ivermectin paste) 1.87% provides effective treatment and control of the following parasites in horses.

Large Strongyles (adults) – Strongylus vulgaris (also early forms in blood vessels), S.edentatus (also tissue stages), S. equinus, Triodontophorus spp. including T. brevicauda and T.serratus, and Craterostomum acuticaudatum; Small Strongyles (adults, including those resistant to some benzimidazole class compounds) – Coronocyclus spp. including C. coronatus, C. labiatus and C. labratus; Cyathostomum spp. including C. catinatum and C. pateratum; Cylicocyclus spp. including C. insigne, C. leptostomum, C. nassatus and C. brevicapsulatus; Cylicodontophorus spp.; Cylicostephanus spp. including C. calicatus, C. goldi, C. longibursatus and C. minutus, and Petrovinema poculatum; Small Strongyles – Fourth-stage larvae; Pinworms (adults and fourth-stage larvae) – Oxyuris equi; Ascarids (adults and third- and fourth-stage larvae) – Parascaris equorum; Hairworms (adults) – Trichostrongylus axei; Large-mouth Stomach Worms (adults) – Habronema muscae; Bots (oral and gastric stages) – Gasterophilus spp. including G. intestinalis and G. nasalis; Lungworms (adults and fourth-stage larvae) – Dictyocaulus arnfieldi; Intestinal Threadworms (adults) – Strongyloides westeri; Summer Sores caused by Habronema and Draschia spp. cutaneous third-stage larvae; Dermatitis caused by neck threadworm microfilariae, Onchocerca sp.

DOSAGE:

This syringe contains sufficient paste to treat one 1250 lb horse at the recommended dose rate of 91 mcg ivermectin per lb (200 mcg/kg) body weight. Each weight marking on the syringe plunger delivers enough paste to treat 250 lb body weight.

Do not underdose. Ensure each animal receives a complete dose based on a current body weight. Underdosing may result in ineffective treatment, and encourage the development of parasite resistance.

ADMINISTRATION:

(1) While holding plunger, turn the knurled ring on the plunger to the right to move it up towards the barrel until the side nearest the barrel aligns with the line at the prescribed weight marking, as shown in the pictogram.

(2) Ensure the ring is secured at the appropriate weight by turning the ring 1/4 turn to the left.

(3) Make sure that the horse’s mouth contains no feed.

(4) Remove the cover from the tip of the syringe.

(5) Insert the syringe tip into the horse’s mouth at the space between the teeth.

(6) Depress the plunger as far as it will go, depositing paste on the back of the tongue.

(7) Immediately raise the horse’s head for a few seconds after dosing.

PARASITE CONTROL PROGRAM: All horses should be included in a regular parasite control program with particular attention being paid to mares, foals and yearlings. Foals should be treated initially at 6 to 8 weeks of age, and routine treatment repeated as appropriate. Consult your
veterinarian for a control program to meet your specific needs. Horse HealthTM (ivermectin paste) 1.87% effectively controls gastrointestinal nematodes and bots of horses. Regular treatment will reduce the chances of verminous arteritis caused by Strongylus vulgaris.

PRODUCT ADVANTAGES: Broad-spectrum Control– Horse HealthTM (ivermectin paste) 1.87% kills important internal parasites, including bots and the arterial stages of S. vulgaris, with a single dose. Horse HealthTM (ivermectin paste) 1.87% is a potent antiparasitic agent that is
neither a benzimidazole nor an organophosphate.

ANIMAL SAFETY: Horse HealthTM (ivermectin paste) 1.87% may be used in horses of all ages, including mares at any stage of pregnancy. Stallions may be treated without adversely affecting their fertility.

WARNINGS

WARNING: Do not use in horses intended for human consumption.
Not for use in humans. Keep this and all drugs out of reach of children.

Refrain from smoking and eating when handling. Wash hands after use. Avoid contact with eyes. The Safety Data Sheet (SDS) contains more detailed occupational safety information. To report adverse reactions in users, to obtain more information, or to obtain an SDS, contact Farnam Companies, Inc. at 800-234-2269.

PRECAUTIONS

PRECAUTIONS: Horse HealthTM (ivermectin paste) 1.87% has been formulated specifically for use in horses ONLY. This product should not be used in other animal species as severe adverse reactions, including fatalities in dogs, may result.

OTHER WARNINGS: Parasite resistance may develop to any dewormer, and has been reported for most classes of dewormers.

Treatment with a dewormer used in conjunction with parasite management practices appropriate to the geographic area and the animal(s) to be treated may slow the development of parasite resistance.

Fecal examinations or other diagnostic tests and parasite management history should be used to determine if the product is appropriate for the herd, prior to the use of any dewormer. Following the use of any dewormer, effectiveness of treatment should be monitored (for example, with the use of a fecal egg count reduction test or another appropriate method).

A decrease in a drug's effectiveness over time as calculated by fecal egg count reduction tests may indicate the development of resistance to the dewormer administered. Your parasite management plan should be adjusted accordingly based on regular monitoring.

ENVIRONMENTAL WARNING

Environmental Safety: Ivermectin and excreted ivermectin residues may adversely affect aquatic organisms. Do not contaminate ground or surface water. Dispose of the syringe in an approved landfill or by incineration.

INFORMATION FOR HORSE OWNERS:

Swelling and itching reactions after treatment with Horse HealthTM (ivermectin paste) 1.87% have occurred in horses carrying heavy infections of neck threadworm (Onchocerca sp.) microfilariae. These reactions were most likely the result of microfilariae dying in large numbers. Symptomatic treatment may be advisable. Consult your veterinarian should any such reactions occur. Healing of summer sores involving extensive tissue changes may require other appropriate therapy in conjunction with treatment with Horse HealthTM (ivermectin paste) 1.87%. Reinfection, and measures for its prevention, should also be considered. Consult your veterinarian if the condition does not improve.

STORAGE AND HANDLING

CONTACT INFORMATION: To report suspected adverse drug events, for technical assistance or to obtain a copy of the SDS, contact Farnam Companies, Inc. at 800-234-2269. For additional information about adverse drug experience reporting for animal drugs, contact FDA at

1-888-FDA-VETS or online at http://www.fda.gov/reportanimalae

STORAGE INFORMATION: Store at 20°C to 25°C (68°F to 77°F), excursions permitted between 15°C - 30°C (between 59°F and 86°F).

©2010-2023 Farnam Companies, Inc. RM: 99.0000276.05 • HH022023-3 Horse Health is a trademark of Farnam Companies, Inc.

Rev. 10/23